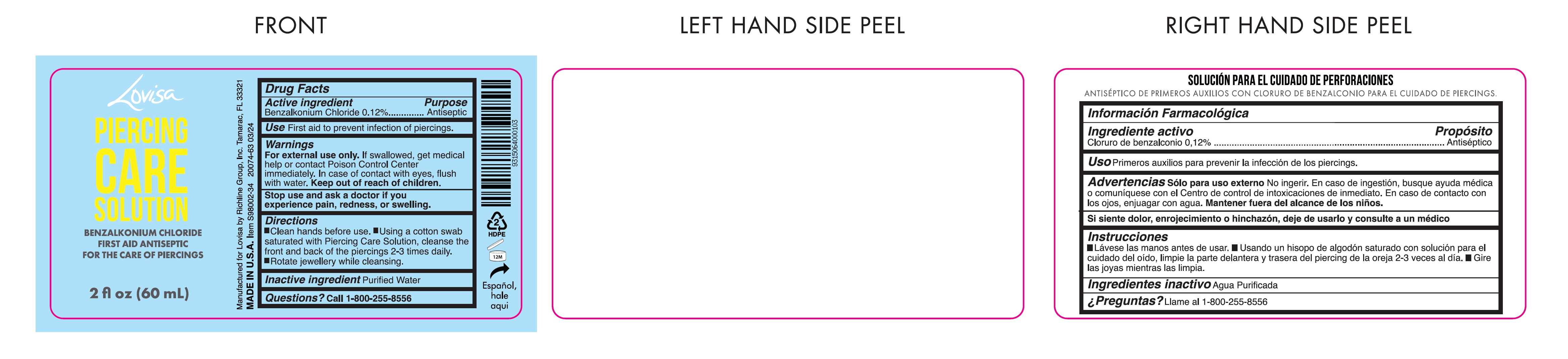 DRUG LABEL: Lovisa Piercing Care Solution
NDC: 70094-006 | Form: LIQUID
Manufacturer: The Richline Group, Inc.
Category: otc | Type: HUMAN OTC DRUG LABEL
Date: 20240418

ACTIVE INGREDIENTS: BENZALKONIUM CHLORIDE 1.2 mg/1 mL
INACTIVE INGREDIENTS: WATER

Lovisa Piercing Care Solution

Active ingredient

Benzalkonium Chloride 0.12%

Purpose

Antiseptic

Use

First aid to prevent infection of pierced ears.

Warnings

For external use only.If swallowed, get medical help or contact Poison Control Center immediately. In case of contact with eyes, flush with water.

Stop use and ask a doctor

if you experience pain, redness, or swelling.

Directions

- Clean hands before use.
- Using a cotton swab saturated with Piercing Care Solution, cleanse the front and back of the piercings 2-3 times daily.
- Rotate jewellery while cleansing.

Inactive ingredient

Purified Water

Questions?

Call 1-800-255-8556